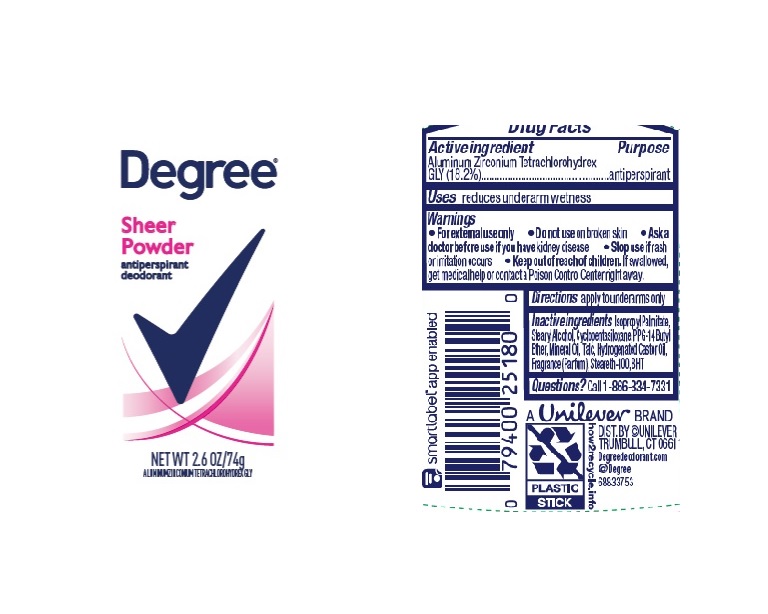 DRUG LABEL: Degree
NDC: 64942-1980 | Form: STICK
Manufacturer: Conopco Inc. d/b/a/ Unilever
Category: otc | Type: HUMAN OTC DRUG LABEL
Date: 20241108

ACTIVE INGREDIENTS: ALUMINUM ZIRCONIUM TETRACHLOROHYDREX GLY 18.2 g/100 g
INACTIVE INGREDIENTS: STEARETH-100; CYCLOMETHICONE 5; HYDROGENATED CASTOR OIL; BUTYLATED HYDROXYTOLUENE; PPG-14 BUTYL ETHER; STEARYL ALCOHOL; TALC; MINERAL OIL; ISOPROPYL PALMITATE

Degree Sheer Powder Antiperspirant Deodorant

Drug Facts

Active ingredient

Aluminum Zirconium Tetrachlorohydrex GLY (18.2)

Purpose

antiperspirant

Uses

reduces underarm wetness

Warnings

• For externaluse only.
• Do not use on broken skin .
• Ask a doctor before use if you have kidney disease.
• Stop use if rash or irritation occurs.

• Keep out of reach of children.

If swallowed, get medical help or contact a Poison Control Center right away.

Directions

apply to underarms only

Inactive ingredients

Isopropyl Palmitate, Stearyl Alcohol, Cyclopentasiloxane, PPG-14 Butyl Ether, Mineral Oil, Talc, Hydrogenated Castor Oil, Fragrance (Parfum), Steareth-100, BHT

Questions?

Call 1-866-334-7331